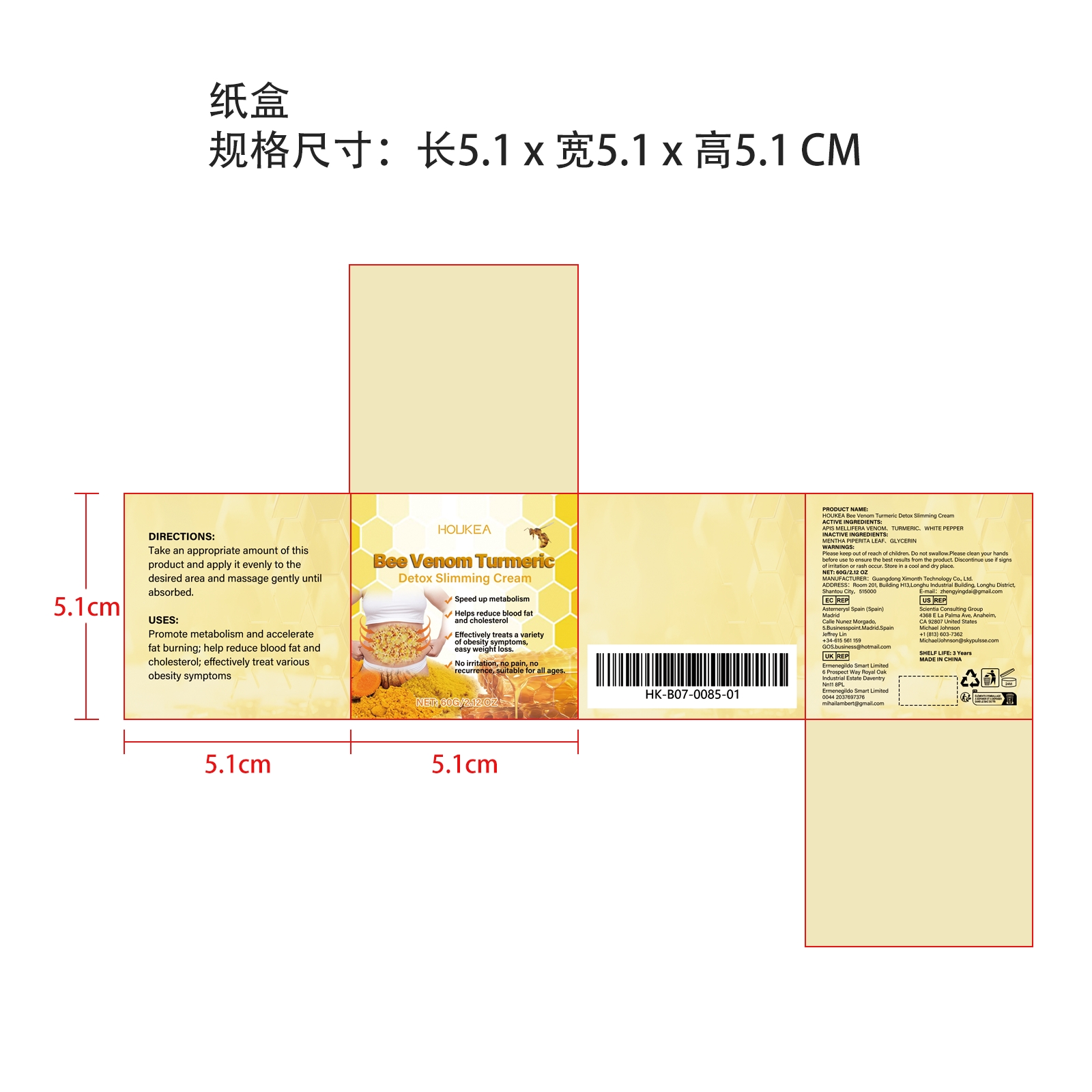 DRUG LABEL: HOUKEA Bee Venom Turmeric Detox Slimming Cream
NDC: 84660-082 | Form: CREAM
Manufacturer: Guangdong Ximonth Technology Co., Ltd.
Category: otc | Type: HUMAN OTC DRUG LABEL
Date: 20241021

ACTIVE INGREDIENTS: APIS MELLIFERA VENOM 12 g/60 g; WHITE PEPPER 6 g/60 g; TURMERIC 9 g/60 g
INACTIVE INGREDIENTS: GLYCERIN 18 g/60 g; MENTHA PIPERITA LEAF 15 g/60 g

Active Ingredient(s)

APIS MELLIFERA VENOM、 TURMERIC、 WHITE PEPPER

Purpose

Promote metabolism and accelerate fat burning; help reduce blood fat and cholesterol; effectively treat various obesity symptoms

Use

Take an appropriate amount of this product and apply it evenly to thedesired area and massage gently until absorbed.

Warnings

Please keep out of reach of children.Do not swallow.Please clean your hands before use to ensure the best results from the product.Discontinue use if signs of irritation or rash occur.Store in a cool and dry place.

Do not use

Discontinue use if signs of irritation or rash occur.

STOP USE

Discontinue use if signs of irritation or rash occur.

KEEP OUT OF REACH OF CHILDREN

Please keep out of reach of children. Do not swallow.

STORAGE AND HANDLING

Avoid freezing and excessive heat above 40C (104F) ）
Store in a cool and dry place.

INACTIVE INGREDIENT

MENTHA PIPERITA LEAF、GLYCERIN